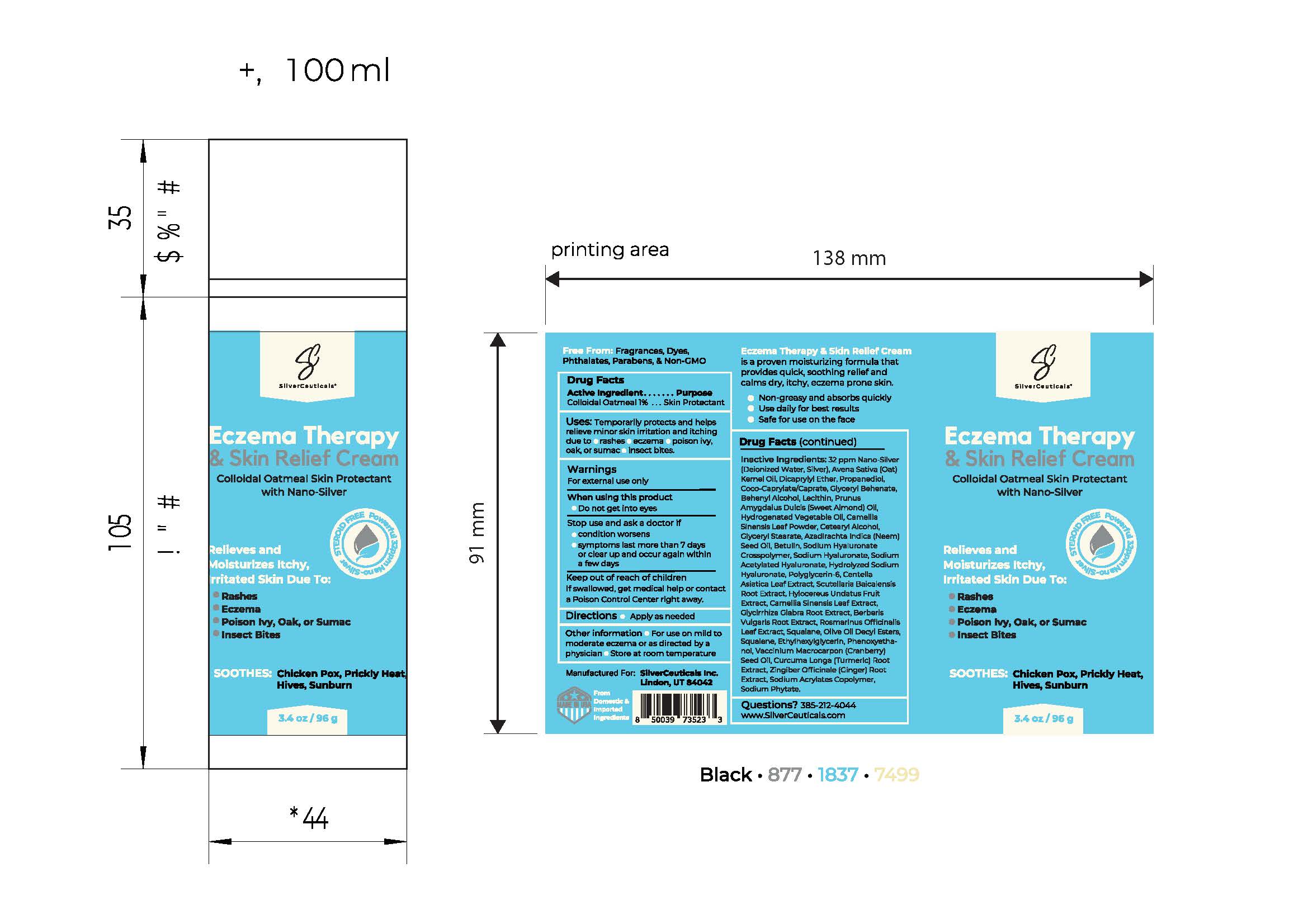 DRUG LABEL: Eczema Therapy
NDC: 85951-010 | Form: CREAM
Manufacturer: SilverCeuticals
Category: otc | Type: HUMAN OTC DRUG LABEL
Date: 20250806

ACTIVE INGREDIENTS: OATMEAL 0.96 g/96 g
INACTIVE INGREDIENTS: HYLOCEREUS UNDATUS FRUIT JUICE; LECITHIN, SOYBEAN; GLYCYRRHIZA GLABRA (LICORICE) RHIZOME/ROOT; BEHENYL ALCOHOL; GLYCERYL 1-STEARATE; GLYCERYL DIBEHENATE; PROPYLENE GLYCOL; COCO-CAPRYLATE/CAPRATE; HYDROGENATED SOYBEAN LECITHIN; WATER; PHENOXYETHANOL; ETHYLHEXYLGLYCERIN; COLLOIDAL SILVER; AVENA SATIVA (OAT) KERNEL OIL; MELIA AZADIRACHTA SEED OIL; CURCUMA LONGA (TURMERIC) ROOT POWDER; ACRYLIC ACID/SODIUM ACRYLATE COPOLYMER (1:1; 600 MPA.S AT 0.2%); SODIUM HYALURONATE; BETULIN; POLYGLYCERIN-6; CENTELLA ASIATICA LEAF; CAMELLIA SINENSIS LEAF; BERBERIS VULGARIS ROOT BARK; GLYCERYL MONOBEHENATE; SCUTELLARIA BAICALENSIS ROOT; ROSMARINUS OFFICINALIS (ROSEMARY) LEAF POWDER; VACCINIUM MACROCARPON (CRANBERRY) SEED OIL; GINGER; DICAPRYLYL ETHER; PROPANEDIOL; SQUALANE; OLIVE OIL DECYL ESTERS; CETYL ALCOHOL

Active Ingredient

Active Ingredient | Purpose
Colloidal Oatmeal 1% | Skin Protectant

Purpose

Skin Protectant

Uses: Temporarly protects adn helps relieve minor skin irration and itching due to:

- rashes
- eczema
- posion ivy
- oak, or sumac
- insect bites

Do not use

Stop use and ask a doctor if

- cconition worsens
- symptons last more than 7 days or clear up and occur again with a few days

Warnings

For external use only

Keep out of reach of children. If swallowed, get medical help or contact Poison Control right away

Instructions for use

Directions

- Apply as needed

Other safety information

Other infromation:

- For use on mild to maderate exzema or as directed by physician
- Store at room temperature

Dosage

Apply as needed

Inactive ingredients

Sodium Nitrite

CoCo Betaine

Deionized Water

Citric Acid

Indications and usage

Directions:

- Clean the affected area
- Apply a small amount of this product on the area once daily
- May be covered with a sterile bandage
- If bandaged, let dry first

Warnings

Warnings: For external use only

Questions

Questions? 385-212-4044